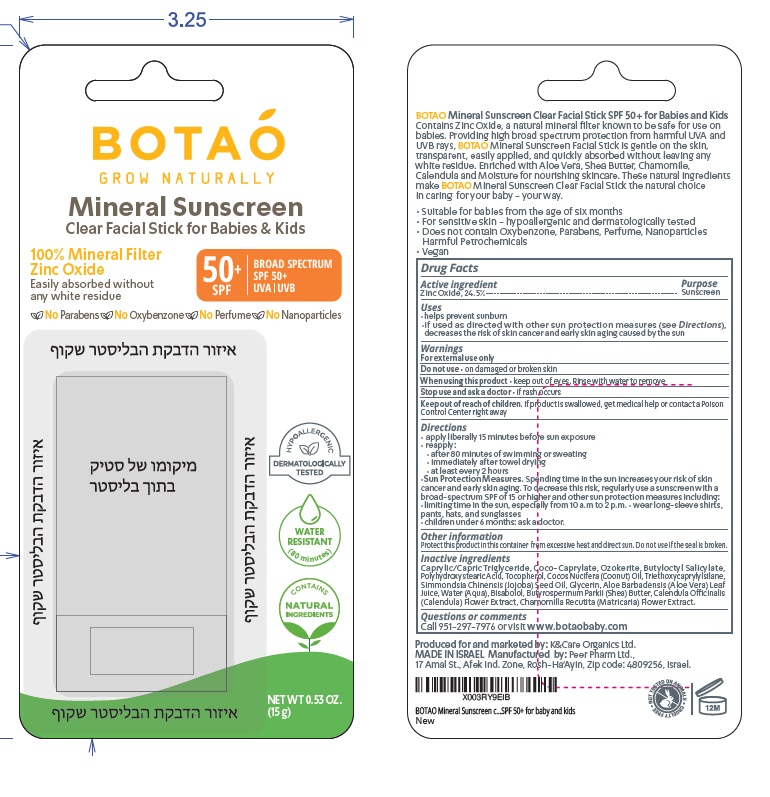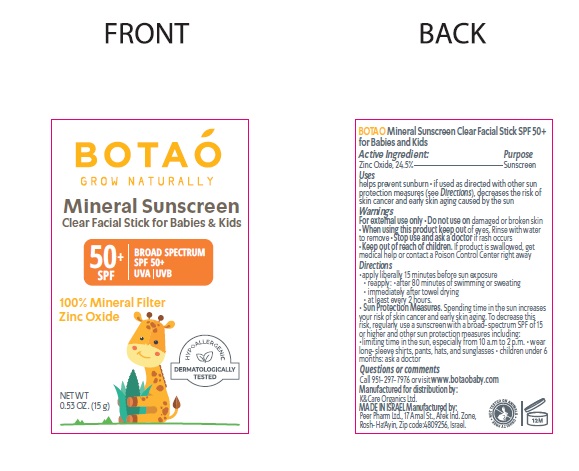 DRUG LABEL: Botao - Grow Naturally Mineral Sunscreen Clear Facial Stick For Babies and Kids SPF 50
NDC: 69435-1508 | Form: STICK
Manufacturer: Peer Pharm Ltd.
Category: otc | Type: HUMAN OTC DRUG LABEL
Date: 20260112

ACTIVE INGREDIENTS: ZINC OXIDE 24.5 g/100 g
INACTIVE INGREDIENTS: MEDIUM-CHAIN TRIGLYCERIDES; COCO-CAPRYLATE; CERESIN; BUTYLOCTYL SALICYLATE; POLYHYDROXYSTEARIC ACID (2300 MW); TOCOPHEROL; COCONUT OIL; TRIETHOXYCAPRYLYLSILANE; JOJOBA OIL; GLYCERIN; ALOE VERA LEAF; WATER; LEVOMENOL; SHEA BUTTER; CALENDULA OFFICINALIS FLOWER; CHAMOMILE

Active Ingredient

Zinc Oxide 24.5 %

Purpose

Sunscreen

Uses

- helps prevent sunburn
- if used as directed with other sun protection measures (see Directions), decreases the risk of skin cancer and early skin aging caused by the sun

warnings

- For external use only
- Do not useon damaged or broken skin
- When using this productkeep out of eyes. Rinse with water to remove
- Stop use and ask a doctor if rash occurs
- Keep out of reach of children. If product is swallowed, get medical help or contact a Poison Control Center right away

Do not use

- on damaged or broken skin.

When using this product,

- Keep out of eyes. Rinse with water to remove.

Stop use and ask a doctor

- if rash or irritation develops and lasts.

Keep out of reach of children.

If swallowed, call a poison control center or get medical help right away.

Directions

- apply liberally 15 minutes before sun exposure

• reapply:
• after 80 minutes of swimming or sweating
• immediately after towel drying
• at least every 2 hours
• Sun Protection Measures. Spending time in the sun increases your risk of skin cancer and early skin aging. To decrease this risk, regularly use a sunscreen with a broad-spectrum SPF of 15 or higher and other sun protection measures including:
•limiting time in the sun, especially from 10 a.m to 2 p.m. • wear long-sleeve shirts, pants, hats, and sunglasses
•children under 6 months: ask a doctor.

Other information

Protect this product in this container from excessive heat and direct sun. Do not use if the seal is broken.

Inactive ingredients

Caprylic/Capric Triglyceride, Coco-Caprylate, Ozokerite, Butyloctyl Salicylate, Polyhydroxystearic Acid, Tocopherol, Cocos Nucifera (Coonut) Oil, Triethoxycaprylylsilane, Simmondsia Chinensis (Jojoba) Seed Oil, Glycerin, Aloe Barbadensis (Aloe Vera) Leaf Juice, Water (Aqua), Bisabolol, Butyrospermum Parkii (Shea) Butter, Calendula Offcinalis(Calendula) Flower Extract, Chamomilla Recutita (Matricaria) Flower Extract.

Questions or comments

Call 951-297-7976 or visit www.botaobaby.com